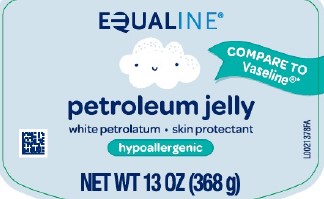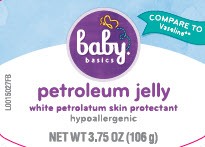 DRUG LABEL: Petroleum
NDC: 41163-069 | Form: JELLY
Manufacturer: United Natural Foods, Inc. dba UNFI
Category: otc | Type: HUMAN OTC DRUG LABEL
Date: 20260216

ACTIVE INGREDIENTS: PETROLATUM 1 g/1 g

Equaline_Baby Basics 069.001/069AA
Petroleum Jelly

Active ingredients

White petrolatum USP (100%)

Purpose

Skin protectant

Uses

- temporarily protects minor: -cuts -scrapes -burns
- temporarily protects and helps relieve chapped or cracked skin and lips
- helps protect from the drying effects of wind and cold weather

Warnings

For external use only

Do not use on

- deep or punture wounds
- animal bites
- serious burns

When using this product

- do not get into eyes

Stop use and ask a doctor if

- condition worsens
- symptoms last more than 7 days or clear up and occur again within a few days

Keep out of reach of children

If swallowed, get medical help or contact a Poison Control Center right away.

Directions

apply as needed

Inactive ingredients

None

Adverse Reactions

DISTRIBUTED BY UNFI

PROVIDENCE, RI 02908

USA

855-423-2630

*This product is not manufactured or distributed Unilever, distributor of Vaseline®.

Principal display panel

EQUALINE®

COMPARE TO VASELINE®*

petroleum jelly

white petroleum - skin protectant

hypoallergenic

NET WT 3.75 OZ (106 g)

Principal display panel

baby basics®

COMPARE TO Vaseline®*

petroleum jelly

white petroleum skin protectant

hypoallergenic

NET WT 3.75 OZ (106 g)